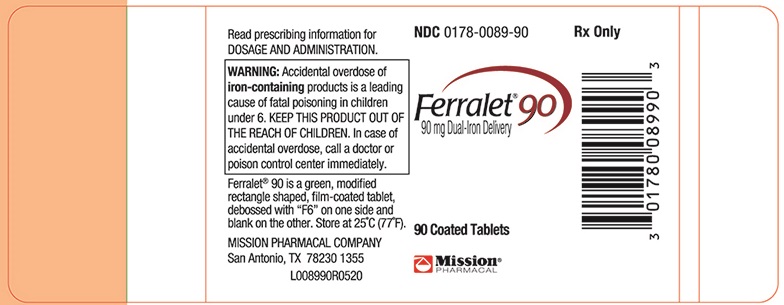 DRUG LABEL: Ferralet 90
NDC: 0178-0089 | Form: TABLET, FILM COATED
Manufacturer: Mission Pharmacal Company
Category: prescription | Type: HUMAN PRESCRIPTION DRUG LABEL
Date: 20260107

ACTIVE INGREDIENTS: IRON 90 mg/1 1; FOLIC ACID 1 mg/1 1; CYANOCOBALAMIN 12 ug/1 1; ASCORBIC ACID 120 mg/1 1; DOCUSATE SODIUM 50 mg/1 1
INACTIVE INGREDIENTS: POVIDONE; CROSCARMELLOSE SODIUM; MAGNESIUM STEARATE; FD&C YELLOW NO. 5; MAGNESIUM SILICATE; FD&C BLUE NO. 1; POLYETHYLENE GLYCOL; VITAMIN A PALMITATE; ETHYL VANILLIN

Ferralet®90
90 mg Dual-Iron Delivery

DESCRIPTION

Each green film-coated tablet for oral administration contains:

Iron (Carbonyl iron, ferrous gluconate) | 90 | mg
Folic Acid 1 | 1 | mg
Vitamin B12(Cyanocobalamin) | 12 | mcg
Vitamin C (Ascorbic acid) | 120 | mg
Docusate sodium 50 | 50 | mg

Inactive Ingredients:Povidone, croscarmellose sodium, acrylic resin, color added, magnesium stearate, FD&C Yellow No. 5, magnesium silicate, FD&C Blue No. 1, polyethylene glycol, vitamin A palmitate, ethyl vanillin.

CLINICAL PHARMACOLOGY

Oral iron is absorbed most efficiently when administered between meals. Iron is critical for normal hemoglobin synthesis to maintain oxygen transport energy production and proper function of cells. Adequate amounts of iron are necessary for effective erythropoiesis. Iron also serves as a cofactor of several essential enzymes, including cytochromes, which are involved in electron transport. Folic acid is required for nucleoprotein synthesis and the maintenance of normal erythropoiesis. Folic acid is the precursor of tetrahydrofolic acid, which is involved as a cofactor for transformylation reactions in the biosynthesis of purines and thymidylates of nucleic acids. Deficiency of folic acid may account for the defective deoxyribonucleic acid (DNA) synthesis that leads to megaloblast formation and megaloblastic macrocytic anemias. Vitamin B12is essential to growth, cell reproduction, hematopoiesis, nucleic acid, and myelin synthesis. Deficiency may result in megaloblastic anemia or pernicious anemia.

INDICATIONS AND USAGE

Ferralet®90 is indicated for the treatment of all anemias that are responsive to oral iron therapy. These include: hypochromic anemia associated with pregnancy, chronic and/or acute blood loss, metabolic disease, postsurgical convalescence, and dietary needs.

CONTRAINDICATIONS

Hypersensitivity to any of the ingredients. Hemolytic anemia, hemochromatosis, and hemosiderosis are contraindications to iron therapy.

WARNING

Folic acid alone is improper therapy in the treatment of pernicious anemia and other megaloblastic anemias where vitamin B12is deficient.

WARNING

Accidental overdose of iron-containingproducts is a leading cause of fatal poisoning in children under 6. KEEP THIS PRODUCT OUT OF THE REACH OF CHILDREN. In case of accidental overdose, call a doctor or poison control center immediately.

PRECAUTIONS

General

Take 2 hours after meals. Do not exceed recommended dose. Discontinue use if symptoms of intolerance appear. The type of anemia and underlying cause or causes should be determined before starting therapy with Ferralet®90 tablets. Ensure Hgb, Hct, reticulocyte count are determined before starting therapy and periodically thereafter during prolonged treatment. Periodically review therapy to determine if it needs to be continued without change or if a dose change is indicated. This product contains FD&C Yellow No. 5 (tartrazine, which may cause allergic-type reactions (including bronchial asthma) in certain susceptible persons. Although the overall incidence of FD&C Yellow No. 5 (tartrazine) sensitivity in the general population is low, it is frequently seen in patients who also have aspirin hypersensitivity.

Folic Acid

Folic acid in doses above 0.1 mg daily may obscure pernicious anemia in that hematologic remission can occur while neurological manifestations remain progressive. Pernicious anemia should be excluded before using these products since folic acid may mask the symptoms of pernicious anemia.

Pediatric Use

Safety and effectiveness in pediatric patients have not been established.

Geriatric Use

Dosing for elderly patients should be cautious. Due to the greater frequency of decreased hepatic, renal, or cardiac function, and of concomitant disease or other drug therapy, dosing should start at the lower end of the dosing range.

ADVERSE REACTIONS

Adverse reactions with iron therapy may include GI irritation, constipation, diarrhea, nausea, vomiting, and dark stools. Adverse reactions with iron therapy are usually transient. Allergic sensitization has been reported following both oral and parenteral administration of folic acid.

DRUG INTERACTIONS

Prescriber should be aware of a number of iron/drug interactions, including antacids, tetracyclines, or fluoroquinolones.

OVERDOSAGE

Symptoms: abdominal pain, metabolic acidosis, anuria, CNS damage, coma, convulsions, death, dehydration, diffuse vascular congestion, hepatic cirrohosis, hypotension, hypothermia, lethargy, nausea, vomiting, diarrhea, tarry stools, melena, hematemesis, tachycardia, hyperglycemia, drowsiness, pallor, cyanosis, lassitude, seizures, and shock.

DOSAGE AND ADMINISTRATION

One tablet daily or as directed by a physician.

NOTICE

Contact with moisture can discolor or erode the tablet.

Do not chew tablet.

HOW SUPPLIED

Ferralet®90 (NDC 0178-0089-90) is a green, modified rectangle shaped, film-coated tablet, debossed with "F6" on one side and blank on the other, and packaged in bottles of 90. Store at 25°C (77°F). Excursions permitted to 15°-30°C (59°-86°F). (See USP Controlled Room Temperature.)

To reporta serious adverse event or obtain product information, call (210) 696-8400.

If you have questions about Ferralet®90 please call: 1 (800) 531-3333

MISSION PHARMACAL COMPANY
San Antonio, TX USA 78230 1355

www.missionpharmacal.com

Copyright © 2020 Mission Pharmacal Company. All rights reserved

L00890R0520

PATIENT INFORMATION

Ferralet® 90
90 mg Dual-Iron Delivery

RX ONLY

THERAPEUTIC
GUIDELINES FOR
THE PATIENT

Some facts you should know about Iron Deficiency Anemia

Iron Deficiency Anemia, or IDA, is a common type of anemia. It's a condition in which blood lacks an adequate supply of healthy red blood cells. These cells carry oxygen to tissues. It is oxygenated blood that gives your body energy and your skin a healthy color.

As the name suggests, Iron Deficiency Anemia results from insufficient iron. Your body needs iron to make a substance called hemoglobin. It's the hemoglobin in red blood cells that enables them to carry oxygen.

What causes IDA?

There are many causes of IDA. These include:

- A diet consistently low in iron
- Blood loss due to heavy menstrual bleeding
- Poor iron absorption from food due to intestinal surgery or diseases of the intestine
- Pregnancy (when the need for iron increases significantly)

Women in general are at higher risk of IDA, not only because they lose blood during menstruation but also because their bodies store less iron.

How common is it?

IDA is a common nutritional deficiency, with women most widely affected. Up to 20% of women have IDA.

What are the symptoms?

Some of the symptoms most commonly associated with IDA are fatigue, weakness, and headache. Symptoms may also include light-headedness, pale skin, shortness of breath, and cold hands and feet, among others. As the body becomes more deficient in iron and anemia worsens, the symptoms worsen as well.

How is IDA diagnosed?

A diagnosis is made primarily through blood tests. The doctor checks your hematocrit, the percentage of your blood volume made up of red blood cells and hemoglobin. A lower than normal hemoglobin level indicates anemia. Also, blood tests for IDA typically include a measurement of ferritin, a protein that helps store iron in your body. When the level of ferritin is low, usually the level of iron is, too. If a patient tests positive for IDA, additional tests may be ordered to identify an underlying cause.

Does IDA lead to health complications?

Mild cases of IDA usually don't cause complications. However, left untreated, IDA can increase in severity and contribute to serious health problems. For example, it may lead to a rapid or irregular heartbeat, a complicated pregnancy that can put the mother at risk for a premature delivery or low-birth-weight baby, and delayed growth in infants and children. The good news is that, because IDA is easily treatable, its potential health consequences are generally avoidable.

How is IDA treated?

It's essential to increase the amount of iron in your diet. Foods rich in iron include meat, fish, poultry, and whole grain breads. However, in most cases of IDA, diet alone isn't enough to correct the problem. Iron supplementation is usually needed for several months. Your doctor has prescribed Ferralet®90, a safe and effective iron supplement to help restore your body's iron to normal levels. Plus, it offers the convenience of once-daily dosing. Together with an iron-rich diet, taking Ferralet®90 every day can make a big difference in helping restore your body's iron, and with it your energy and overall feeling of well-being.

PRINCIPAL DISPLAY PANEL - 90 mg Tablet Bottle Label

NDC0178-0089-90

Rx Only

Ferralet® 90
90 mg Dual-Iron Delivery

90 Coated Tablets

MISSION®PHARMACAL